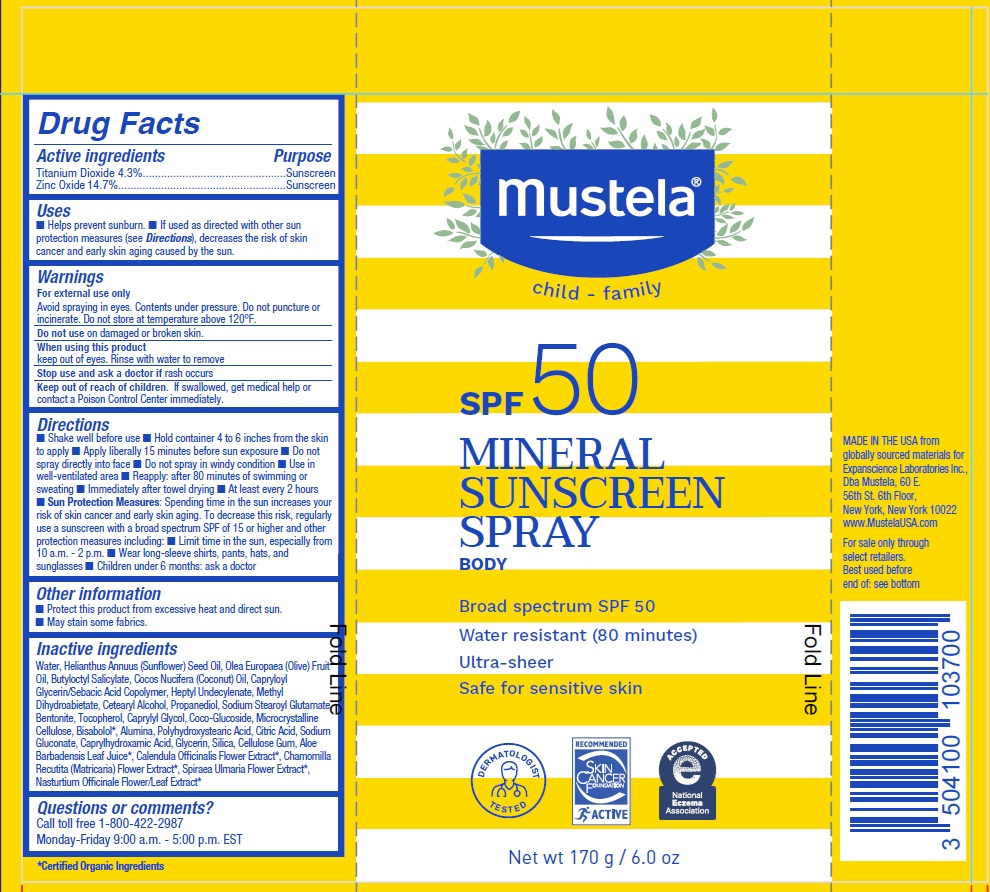 DRUG LABEL: MUSTELA MINERAL SUNSCREEN BROAD SPECTRUM SPF 50
NDC: 64768-2927 | Form: SPRAY
Manufacturer: Expanscience Laboratories d/b/a Mustela
Category: otc | Type: HUMAN OTC DRUG LABEL
Date: 20241202

ACTIVE INGREDIENTS: ZINC OXIDE 147 mg/1 g; TITANIUM DIOXIDE 43 mg/1 g
INACTIVE INGREDIENTS: HEPTYL UNDECYLENATE; METHYL DIHYDROABIETATE; CETOSTEARYL ALCOHOL; BENTONITE; CAPRYLYL GLYCOL; COCO GLUCOSIDE; ALUMINUM OXIDE; SODIUM GLUCONATE; CAPRYLHYDROXAMIC ACID; GLYCERIN; CITRIC ACID MONOHYDRATE; CHAMOMILE; POLYHYDROXYSTEARIC ACID (2300 MW); LEVOMENOL; NASTURTIUM OFFICINALE FLOWERING TOP; SUNFLOWER OIL; FILIPENDULA ULMARIA FLOWER; CALENDULA OFFICINALIS FLOWER; CARBOXYMETHYLCELLULOSE SODIUM, UNSPECIFIED FORM; TOCOPHEROL; WATER; OLIVE OIL; COCONUT OIL; CAPRYLOYL GLYCERIN/SEBACIC ACID COPOLYMER (2000 MPA.S); BUTYLOCTYL SALICYLATE; ALOE VERA LEAF; PROPANEDIOL; SODIUM STEAROYL GLUTAMATE; MICROCRYSTALLINE CELLULOSE; SILICON DIOXIDE

MUSTELA MINERAL SUNSCREEN SPRAY BROAD SPECTRUM SPF 50

Active ingredients

Titanium Dioxide 4.3%

Zinc Oxide 14.7%

Purpose

Sunscreen

Uses

- Helps prevent sunburn
- If used as directed with other sun protection measures (see Directions), decreases the risk of skin cancer and early skin aging caused by the sun.

Warnings

For external use only

Avoid spraying in eyes. Contents under pressure. Do not puncture or incinerate. Do not store at temperature above 120F.

Do not use

on damaged or broken skin

When using this product

keep out of eyes. Rinse with water to remove

Stop use and ask a doctor

if rash occurs

Keep out of reach of children.

If swallowed, get medical help or contact a Poison Control Center immediately.

Directions

- Shake well before use
- Hold container 4 to 6 inches from the skin to apply
- Apply liberally 15 minutes before sun exposure
- Do not spray directly into face
- Do not spray in windy condition
- Use in well-ventilated area
- Reapply: after 80 minutes of swimming or sweating
- immediately after towel drying
- At least every 2 hours.
- Sun Protection Measures: Spending time in the sun increases your risk of skin cancer and early skin aging. To decrease this risk, regularly use a sunscreen with a broad spectrum SPF of 15 or higher and other protection measures including:
- Limit time in the sun, especially from 10 a.m - 2p.m
- Wear long-sleeved shirt, pants, hat, and sunglasses
- Children under 6 months: ask a doctor.

Other information

- Protect this product from excessive heat and direct sun.
- May stain some fabrics.

Inactive ingredients

Water, Helianthus Annuus (Sunflower) Seed Oil, Olea Europaea (Olive) Fruit Oil, Butyloctyl Salicylate, Cocos Nucifera (Coconut) Oil, Capryloyl Glycerin/Sebacic Acid Copolymer, Heptyl Undecylenate, Methyl Dihydroabietate, Cetearyl Alcohol, Propanediol, Sodium Stearoyl Glutamate, Bentonite, Tocopherol, Caprylyl Glycol, Coco-Glucoside, Microcrystalline Cellulose, Bisabolol*, Alumina, Polyhydroxystearic Acid, Citric Acid, Sodium Gluconate, Caprylhydroxamic Acid, Glycerin, Silica, Cellulose Gum, Aloe Barbadensis Leaf Juice*, Calendula Officinalis Flower Extract*, Chamomilla Recutita (Matricaria) Flower Extract*, Spiraea Ulmaria Flower Extract*, Nasturtium Officinale Flower/Leaf Extract*, *Certified Organic Ingredients

Questions or comments?

Call toll free 1-800-422-2987
Monday-Friday 9:00am-5:00pm EST

Company Information

MADE IN THE USA from globally sourced materials for
Expanscience Laboratories Inc.,
Dba Mustela, 60 E. 56th St. 6th Floor, New York, New York 10022
www.MustelaUSA.com